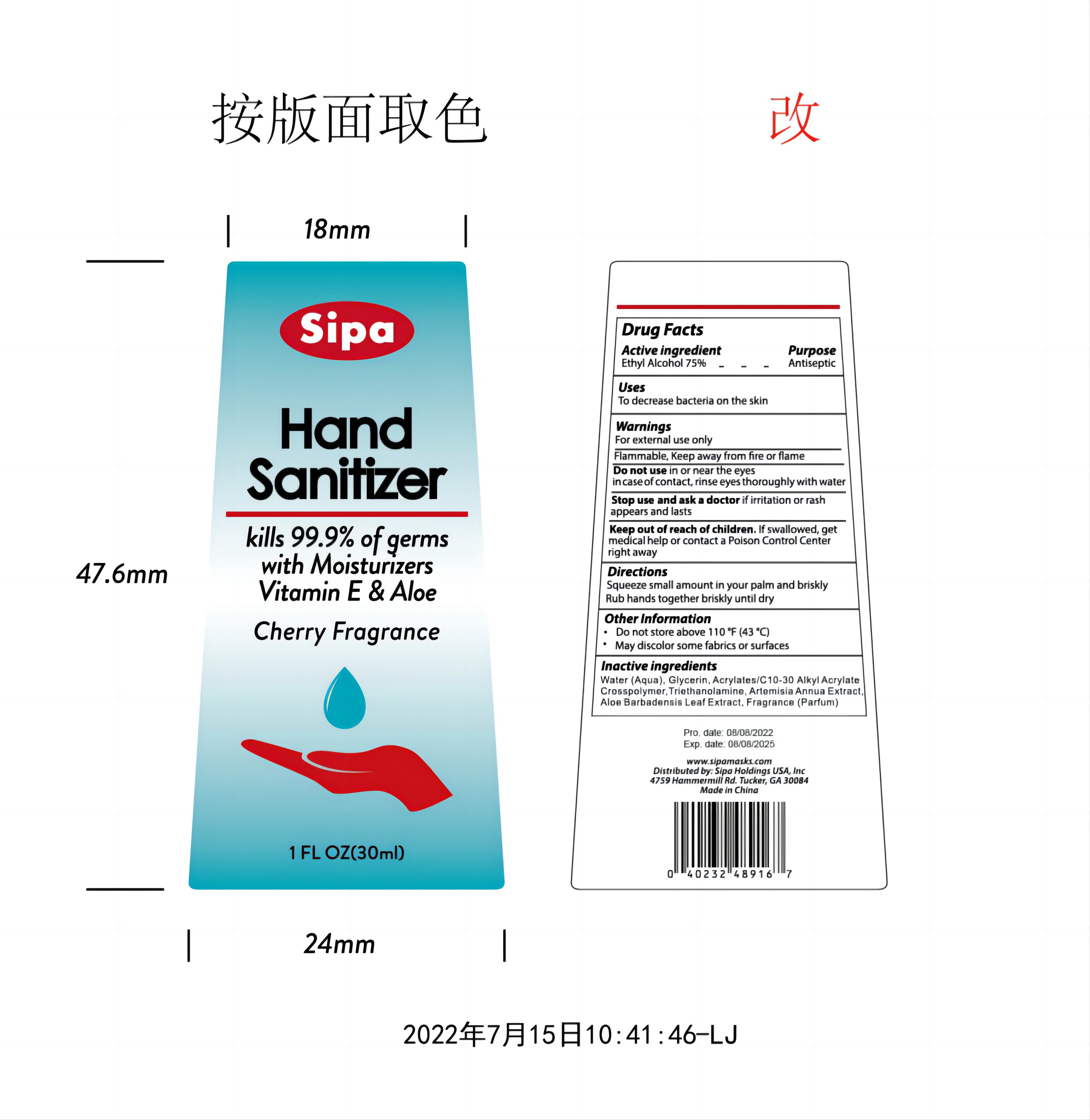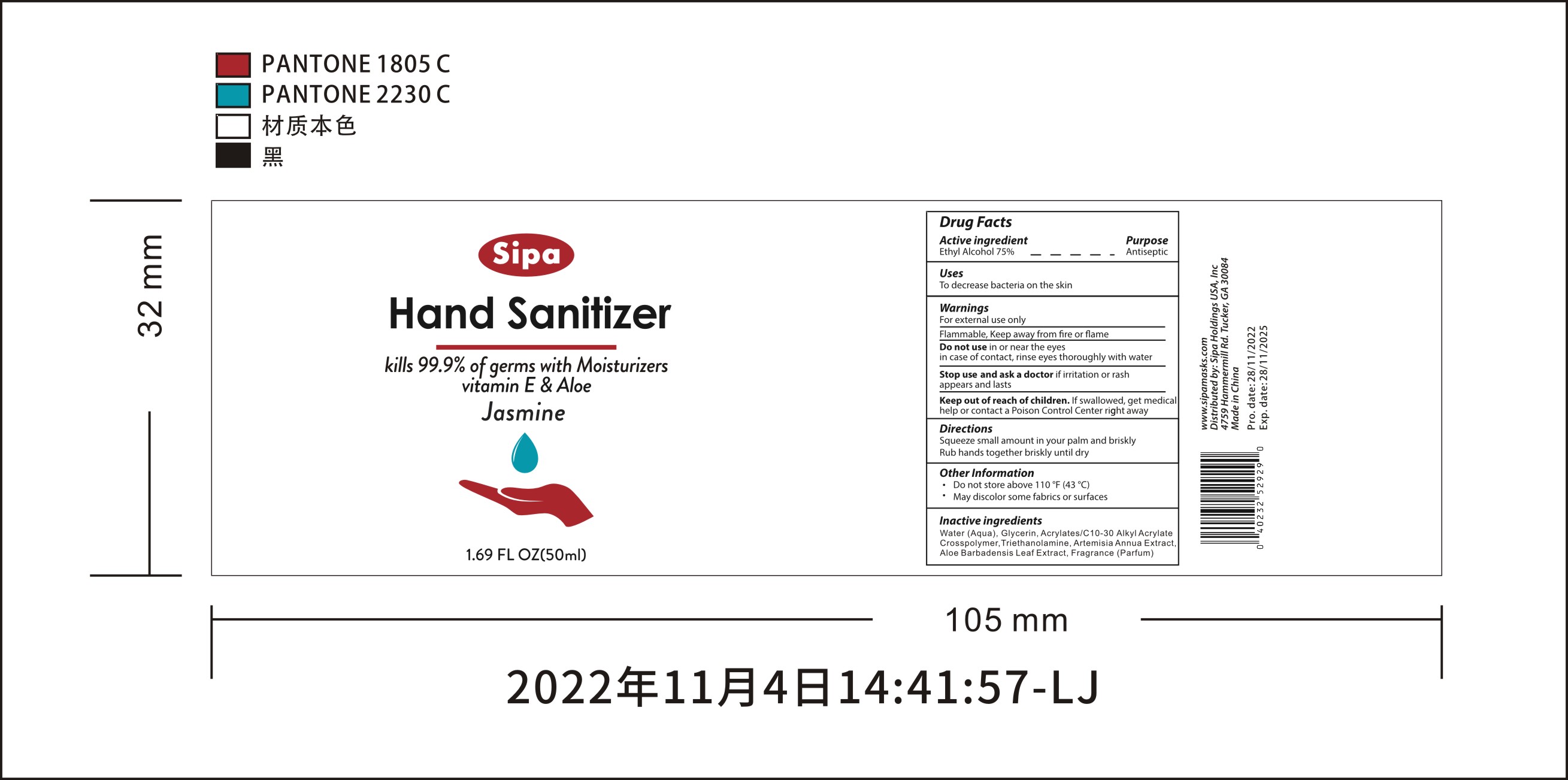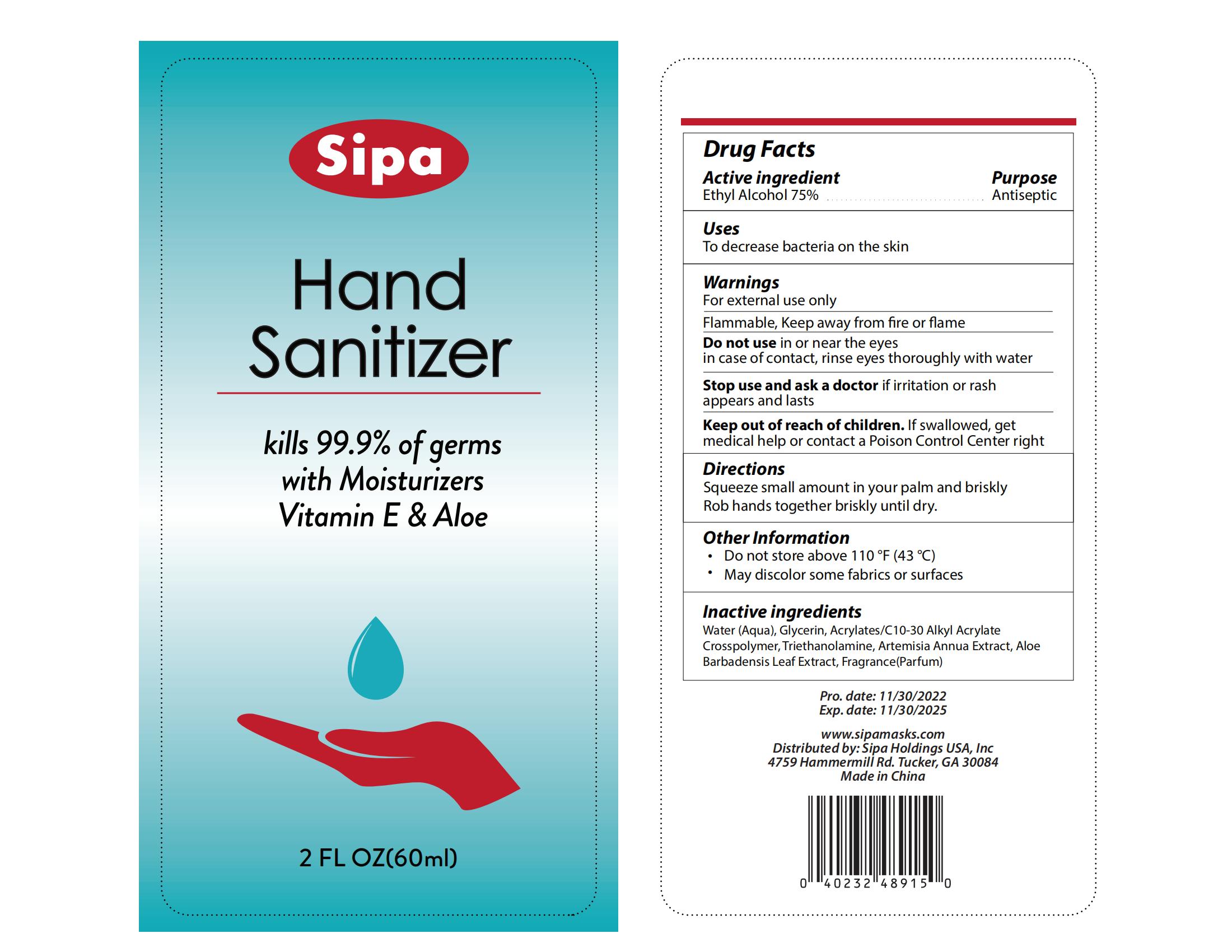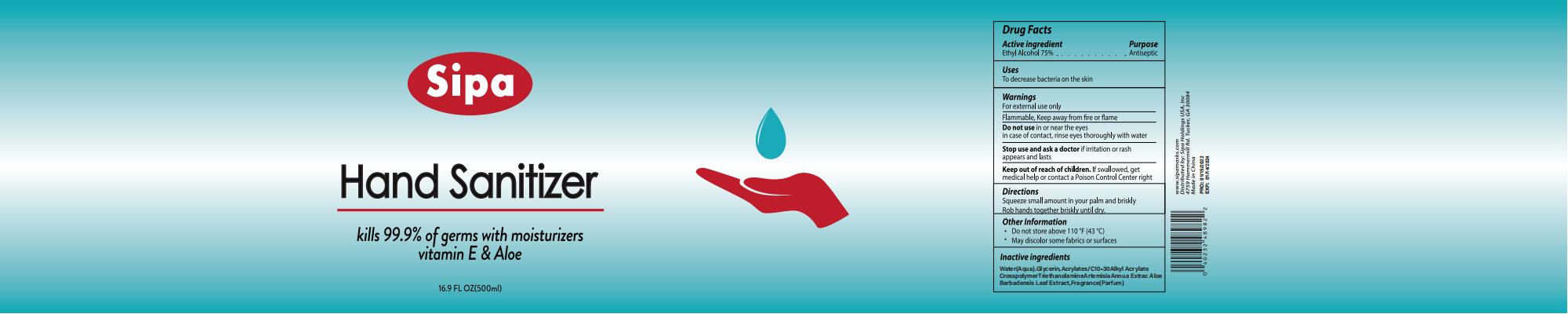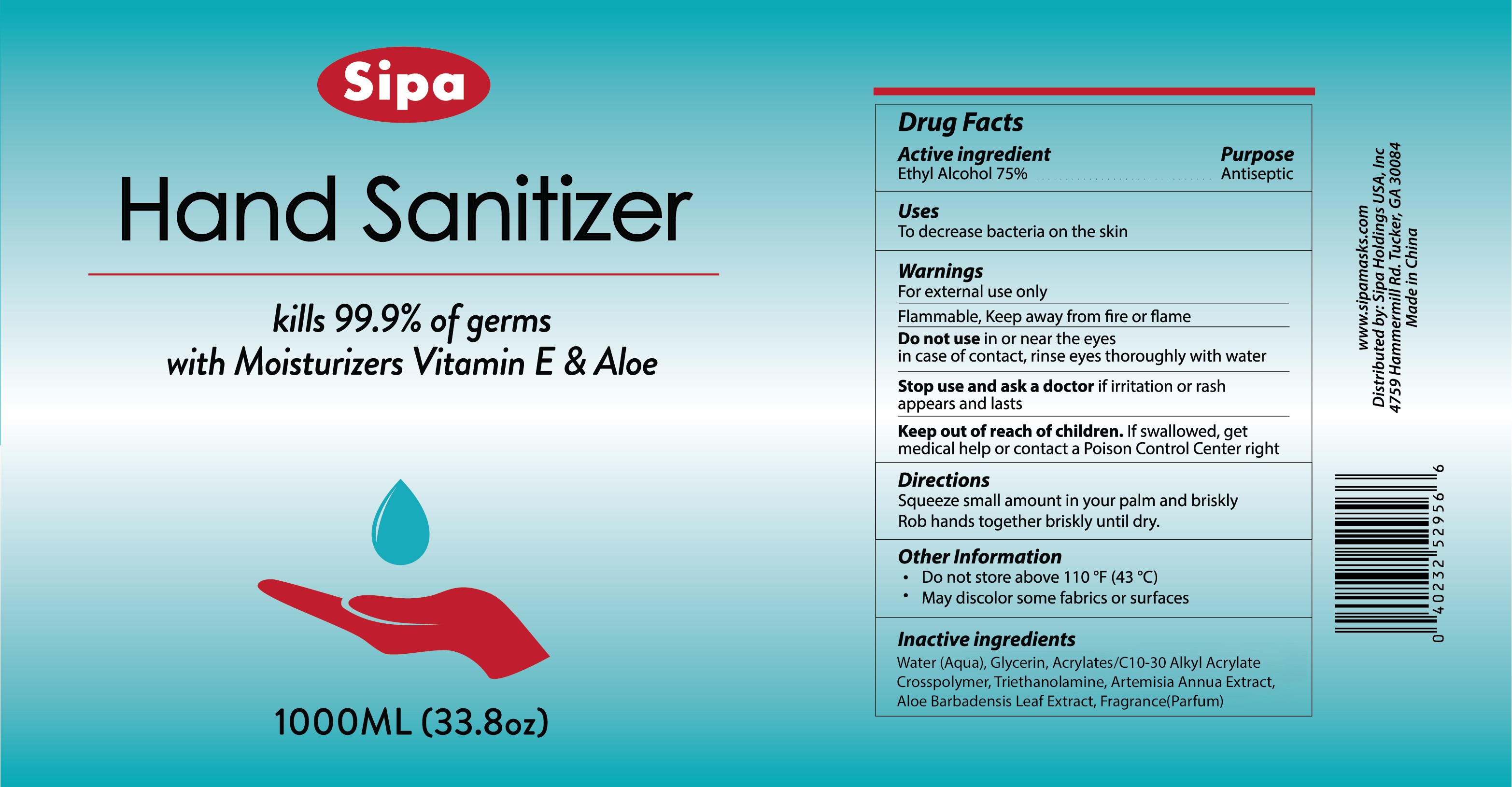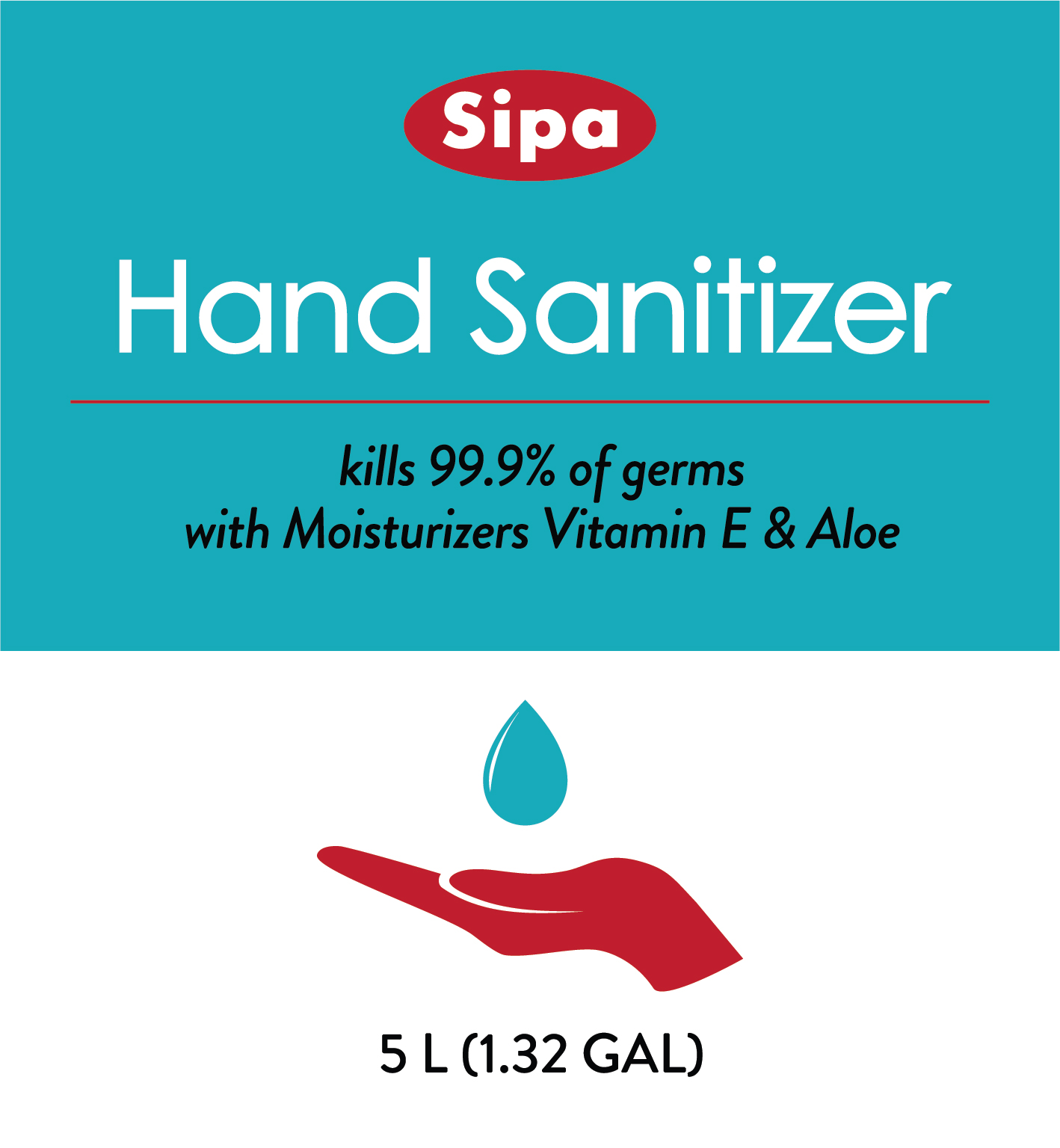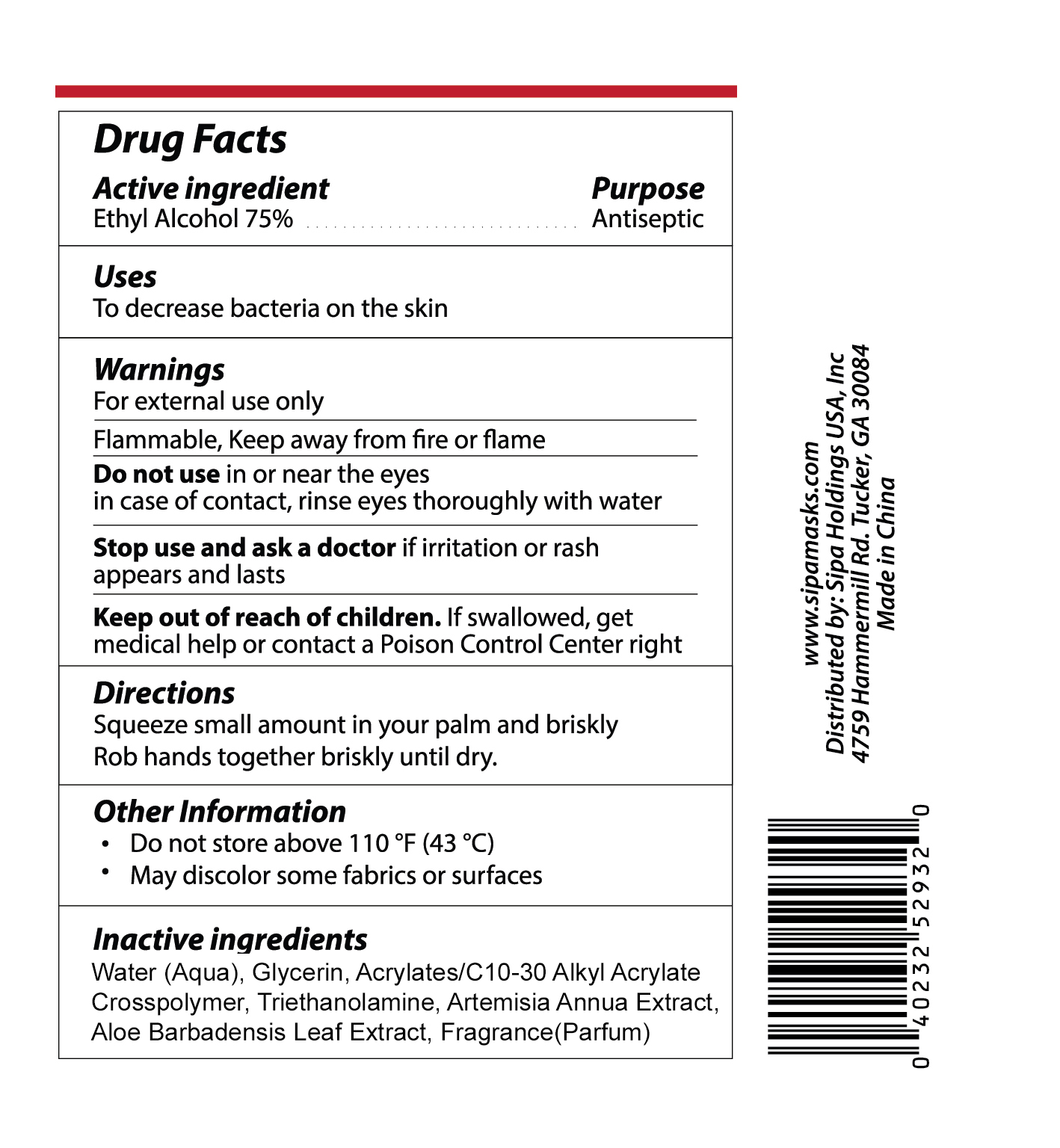 DRUG LABEL: Sipa hand sanitizer with Moisturizers
NDC: 83502-002 | Form: LIQUID
Manufacturer: Tourel (Changsha)Hotel Supplies Co.,Ltd
Category: otc | Type: HUMAN OTC DRUG LABEL
Date: 20250107

ACTIVE INGREDIENTS: ALCOHOL 75 mL/100 mL
INACTIVE INGREDIENTS: TROLAMINE; ALLYL METHACRYLATE/GLYCOL DIMETHACRYLATE CROSSPOLYMER; ARTEMISIA ANNUA LEAF; ALOE VERA LEAF; GLYCERIN; CARBOMER 1342; WATER

83502-002 Update

Active Ingredient

Ethyl Alcohol 75%

Purpose

For hand sanitizing to decrease bacteria on the skin

Use

To decrease bacteria on the skin

Warnings

For external use only
Flammable, Keep away from fire or flame

Do not use

in or near the eyes in case of contact, rinse eyes thoroughly with water

When Using

Pay attention to the method of use. do not touch eyes

Stop Use

if irritation or rashappears and lasts

Ask Doctor

if irritation or rashappears and lasts

Keep Oot Of Reach Of Children

lf swallowed, getmedical help or contact a Poison Control Center right

Directions

Squeeze small amount in your palm and brisklyRob hands together briskly until dry.

Inactive ingredients

Water (Aqua), Glycerin, Acrylates/C10-30 Alkyl AcrylateCrosspolymer,Triethanolamine, Artemisia Annua Extract, AloeBarbadensis Leaf Extract, Fragrance(Parfum)